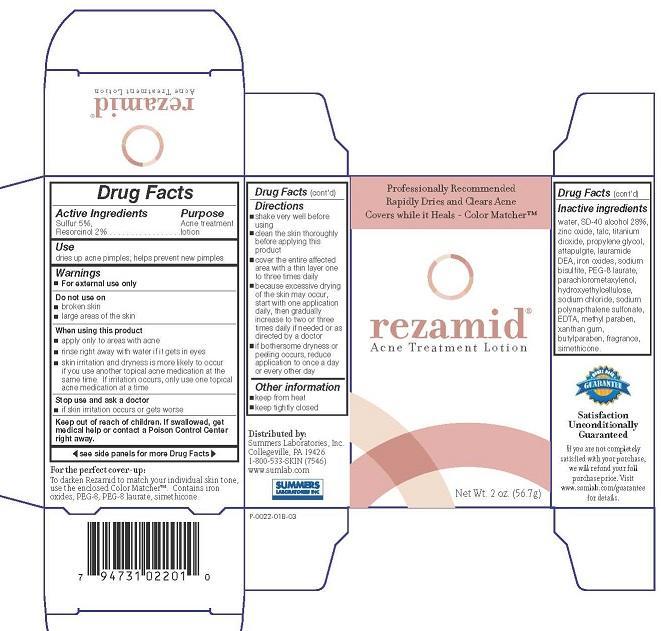 DRUG LABEL: REZAMID
NDC: 11086-022 | Form: LOTION
Manufacturer: Summers Laboratories Inc
Category: otc | Type: HUMAN OTC DRUG LABEL
Date: 20231009

ACTIVE INGREDIENTS: SULFUR 5 g/100 mL; RESORCINOL 2 g/100 mL
INACTIVE INGREDIENTS: WATER; ALCOHOL; ZINC OXIDE; TALC; TITANIUM DIOXIDE; PROPYLENE GLYCOL; ATTAPULGITE; LAURIC DIETHANOLAMIDE; FERRIC OXIDE RED; SODIUM BISULFITE; PEG-8 LAURATE; CHLOROXYLENOL; HYDROXYETHYL CELLULOSE (140 MPA.S AT 5%); SODIUM CHLORIDE; SODIUM NAPHTHALENESULFONATE; EDETIC ACID; METHYLPARABEN; XANTHAN GUM; BUTYLPARABEN; DIMETHICONE; SILICON

SUMMERS LABS (as PLD) - REZAMID (11086-022)

ACTIVE INGREDIENTS

SULFUR 5%

RESORCINOL 2%

PURPOSE

ACNE TREATMENT LOTION

USE

DRIES UP ACNE PIMPLES, HELPS PREVENT NEW PIMPLES

WARNINGS

- FOR EXTERNAL USE ONLY

DO NOT USE

- ON BROKEN SKIN
- ON LARGE AREAS OF THE BODY

WHEN USING THIS PRODUCT

- APPLY TO AFFECTED AREAS ONLY
- DO NOT GET INTO EYES
- skin irritation and dryness is more likely to occur if you use another topical acne medication at the same time. If irritation occurs, only use one topical acne medication at a time

STOP USE AND ASK A DOCTOR IF

- IF SKIN IRRITATION OCCURS OR GETS WORSE

KEEP OUT OF REACH OF CHILDREN. IF SWALLOWED, GET MEDICAL HELP OR CONTACT A POISON CONTROL CENTER RIGHT AWAY.

DIRECTIONS

- shake very well before using
- clean the skin thoroughly before applying this product
- cover the entire affected area with a thin layer one to three times daily
- because excessive drying of the skin may occur, start with one application daily, then gradually increase to two or three times daily if needed or as directed by a doctor
- if bothersome dryness or peeling occurs, reduce application to once a day or every other day

INACTIVE INGREDIENTS

water, SD-40 alcohol 28%, zinc oxide, talc, titanium dioxide, propylene glycol, attapulgite, lauramide DEA, iron oxides, sodium bisulfite, PEG-8 laurate, parachlorometaxylenol, hydroxyethylcellulose, sodium chloride, sodium polynapthalene sulfonate, EDTA, methyl paraben, xanthan gum, butylparaben, fragrance, simethicone.